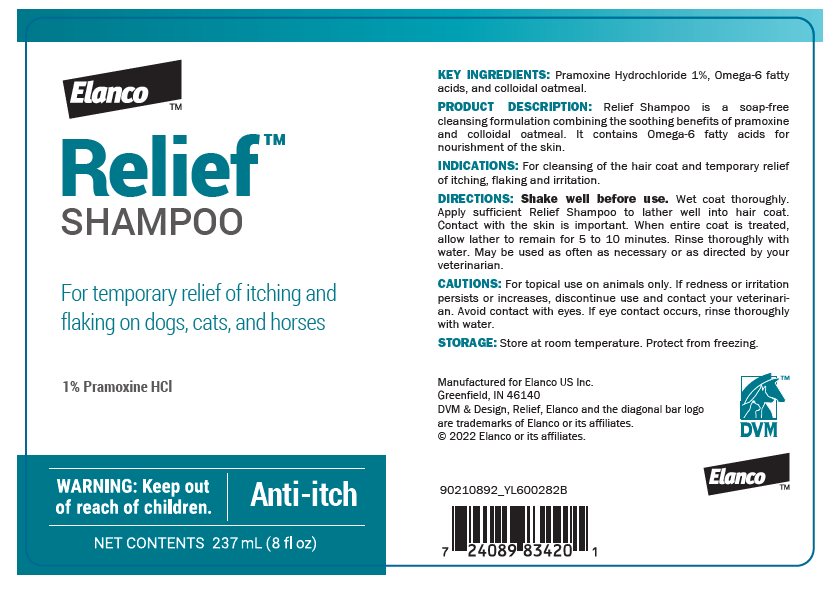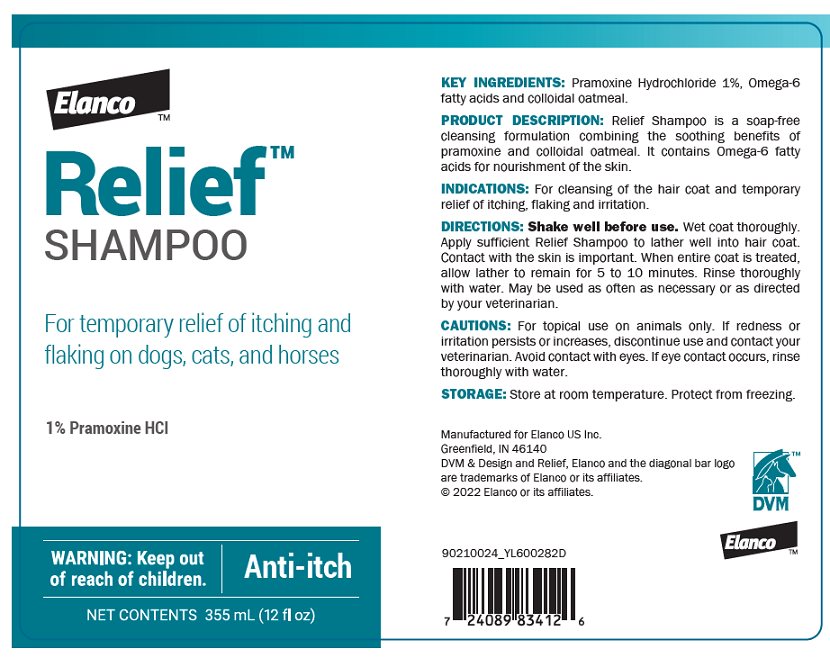 DRUG LABEL: Relief
NDC: 58198-0015 | Form: SHAMPOO
Manufacturer: Elanco US Inc.
Category: animal | Type: OTC ANIMAL DRUG LABEL
Date: 20230412

ACTIVE INGREDIENTS: PRAMOXINE HYDROCHLORIDE 10.8 mg/1 mL

KEY INGREDIENTS: Pramoxine Hydrochloride 1%, Omega-6 fatty acids, and colloidal oatmeal.

DESCRIPTION

PRODUCT DESCRIPTION: Relief Shampoo is a soap-free cleansing formulation combining the soothing benefits of pramoxine and colloidal oatmeal. It contains Omega-6 fatty acids for nourishment of the skin.

INDICATIONS AND USAGE

INDICATIONS: For cleansing of the hair coat and temporary relief of itching, flaking and irritation.

DOSAGE AND ADMINISTRATION

DIRECTIONS: Shake well before use. Wet coat thoroughly. Apply sufficient Relief Shampoo to lather well into hair coat. Contact with the skin is important. When entire coat is treated, allow lather to remain for 5 to 10 minutes. Rinse thoroughly with water. May be used as often as necessary or as directed by your veterinarian.

CAUTIONS: For topical use on animals only. If redness or irritation persists or increases, discontinue use and contact your veterinarian. Avoid contact with eyes. If eye contact occurs, rinse thoroughly with water.

STORAGE: Store at room temperature. Protect from freezing.

Manufactured for Elanco US Inc.
Greenfield, IN 46140
DVM & Design, Relief, Elanco and the diagonal bar logo
are trademarks of Elanco or its affiliates.
© 2022 Elanco or its affiliates.

DVM™

Elanco™

90210892_YL600282B
90210024_YL600282D

Principal Display Panel – 237 mL Bottle Label

Elanco™

Relief™
SHAMPOO

For temporary relief of itching and
flaking on dogs, cats, and horses

1% Pramoxine HCl

WARNING: Keep out of reach of children.

Anti-itch

NET CONTENTS 237 mL (8 fl oz)

Principal Display Panel – 355 mL Bottle Label

Elanco™

Relief™
SHAMPOO

For temporary relief of itching and
flaking on dogs, cats, and horses

1% Pramoxine HCI

WARNING: Keep out of reach of children.

Anti-itch

NET CONTENTS 355 mL (12 fl oz)